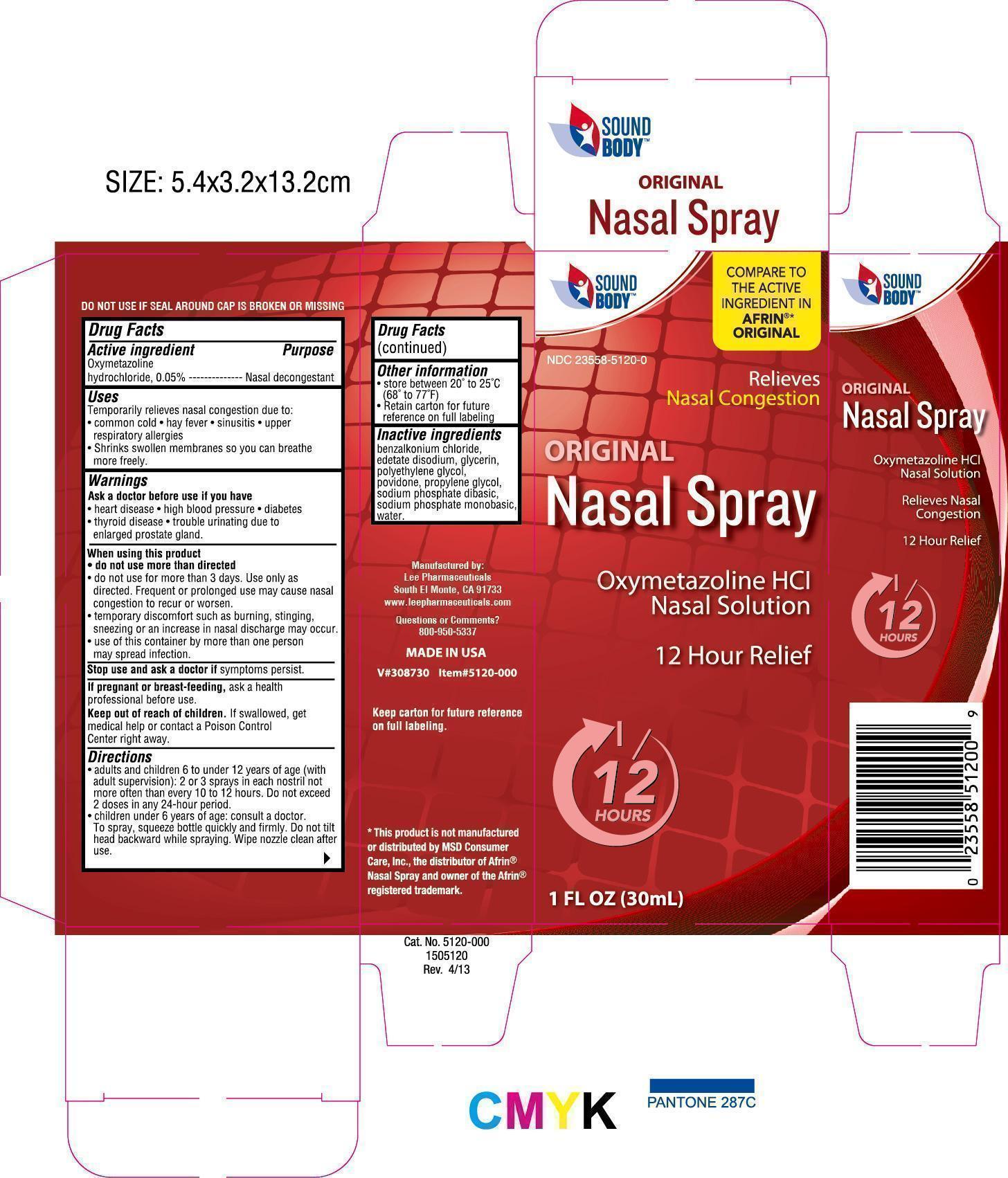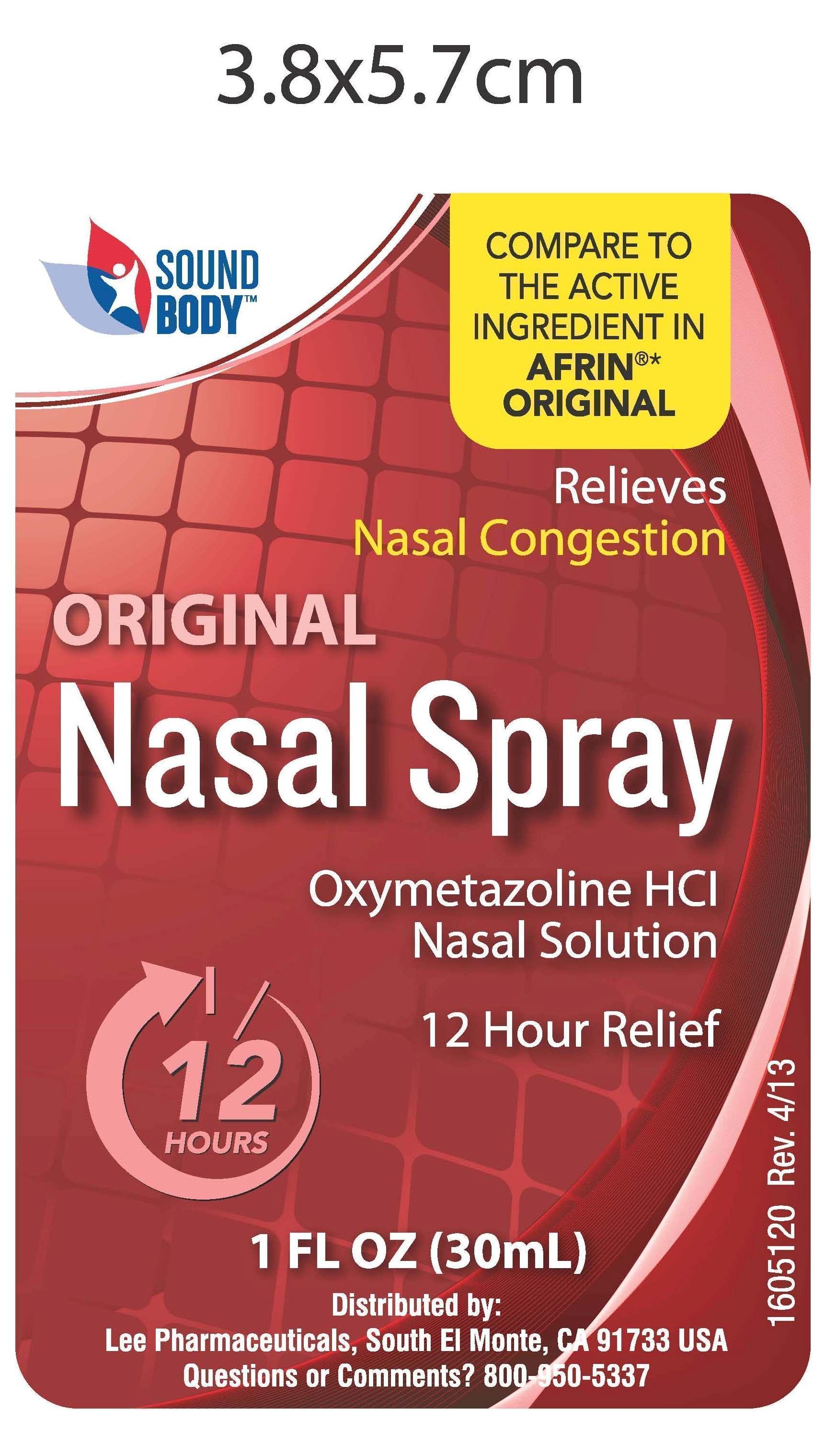 DRUG LABEL: Sound Body 12 Hour Nasal
NDC: 23558-5120 | Form: SPRAY
Manufacturer: Lee Pharmaceuticals
Category: otc | Type: HUMAN OTC DRUG LABEL
Date: 20130619

ACTIVE INGREDIENTS: OXYMETAZOLINE HYDROCHLORIDE 50.0 mg/100.0 mL
INACTIVE INGREDIENTS: BENZALKONIUM CHLORIDE; EDETATE DISODIUM ANHYDROUS; GLYCERIN; POLYETHYLENE GLYCOL 3350; POVIDONE; PROPYLENE GLYCOL; SODIUM PHOSPHATE, DIBASIC; SODIUM PHOSPHATE, MONOBASIC; WATER

Drug Facts

Active ingredient

Oxymetazoline Hydrochloride, 0.05%

Purpose

Nasal Decongestant

Uses

- Temporarily relieves nasal congestion due to: common cold, hay fever, sinusitis, upper respiratory allergies.
- Shrinks swollen membranes so you can breathe more freely.

Ask a doctor before use if you have

- Heart disease
- High blood pressure
- Diabetes
- Thyroid disease
- Trouble urinating due to an enlarged prostate gland

When using this product

- Do not use more than directed
- Do not use for more than 3 days. Use only as directed. Frequent or prolonged use may cause nasal congestion to recur or worsen.
- Temporary discomfort such as burning, stinging, sneezing or an increase in nasal discharge may occur.
- Use of this container by more than one person may spread infection.

Stop use and ask a doctor if symptoms persists.

PREGNANCY OR BREAST FEEDING

If pregnant or breast-feeding, ask a health professional before use.

Keep out of reach of children. If swallowed, get medical help or contact a Poison Control Center right away.

Directions

- Adults and children 6 to under 12 years of age (with adult supervision): 2 or 3 sprays in each nostril not more ofter than every 10 to 12 hours. Do not exceed 2 doses in any 24-hour period.
- Children under 6 years of age: consult a doctor.
- To spray, squeeze bottle quickly and firmly. Do not tilt head backwards while spraying. Wipe nozzle clean after use.

Other information

- Store between 20° - 25° C (68° - 77° F)
- Retain carton for future reference on full labeling.

Inactive ingredients

Benzalkonium chloride, edetate disodium, glycerin, polyethylene glycol, povidone, propylene glycol, sodium phosphate dibasic, sodium phosphate monobasic, water